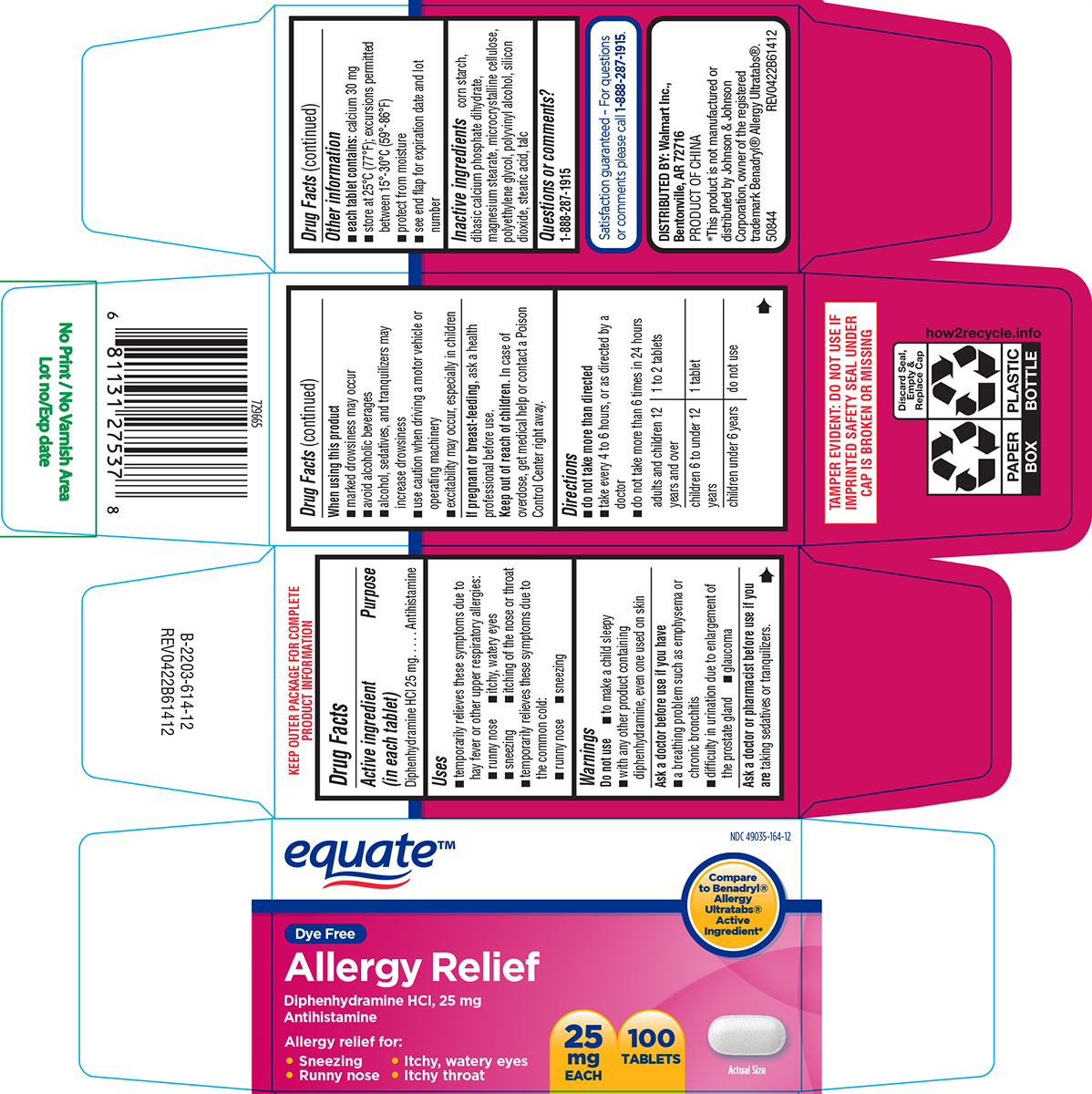 DRUG LABEL: Allergy Relief
NDC: 49035-164 | Form: TABLET, FILM COATED
Manufacturer: Wal-Mart Stores Inc
Category: otc | Type: HUMAN OTC DRUG LABEL
Date: 20250528

ACTIVE INGREDIENTS: DIPHENHYDRAMINE HYDROCHLORIDE 25 mg/1 1
INACTIVE INGREDIENTS: STARCH, CORN; DIBASIC CALCIUM PHOSPHATE DIHYDRATE; MAGNESIUM STEARATE; MICROCRYSTALLINE CELLULOSE; POLYETHYLENE GLYCOL, UNSPECIFIED; POLYVINYL ALCOHOL, UNSPECIFIED; SILICON DIOXIDE; STEARIC ACID; TALC

Equate 44-614 Delisted

Active ingredient (in each tablet)

Diphenhydramine HCl 25 mg

Purpose

Antihistamine

Uses

- temporarily relieves these symptoms due to hay fever or other upper respiratory allergies:
  - runny nose
  - itchy, watery eyes
  - sneezing
  - itching of the nose or throat
- temporarily relieves these symptoms due to the common cold:
  - runny nose
  - sneezing

Warnings

Do not use

- to make a child sleepy
- with any other product containing diphenhydramine, even one used on skin

Ask a doctor before use if you have

- a breathing problem such as emphysema or chronic bronchitis
- difficulty in urination due to enlargement of the prostate gland
- glaucoma

Ask a doctor or pharmacist before use if you are

taking sedatives or tranquilizers.

When using this product

- marked drowsiness may occur
- avoid alcoholic beverages
- alcohol, sedatives, and tranquilizers may increase drowsiness
- use caution when driving a motor vehicle or operating machinery
- excitability may occur, especially in children

If pregnant or breast-feeding,

ask a health professional before use.

Keep out of reach of children.

In case of overdose, get medical help or contact a Poison Control Center right away.

Directions

- do not take more than directed
- take every 4 to 6 hours, or as directed by a doctor
- do not take more than 6 times in 24 hours

adults and children 12 years and over | 1 to 2 tablets
children 6 to under 12 years | 1 tablet
children under 6 years | do not use

Other information

- each tablet contains: calcium 30 mg
- store at 25°C (77°F); excursions permitted between 15°-30°C (59°-86°F)
- protect from moisture
- see end flap for expiration date and lot number

Inactive ingredients

corn starch, dibasic calcium phosphate dihydrate, magnesium stearate, microcrystalline cellulose, polyethylene glycol, polyvinyl alcohol, silicon dioxide, stearic acid, talc

Questions or comments?

1-888-287-1915

Principal display panel

equate™

NDC 49035-164-12

Compare to Benadryl® Allergy Ultratabs® Active Ingredient*

Dye Free
Allergy Relief
Diphenhydramine HCI, 25 mg
Antihistamine

Allergy relief for:
• Sneezing • Itchy, watery eyes
• Runny nose • Itchy throat

25
mg
EACH

100
TABLETS

Actual Size

TAMPER EVIDENT: DO NOT USE IF
IMPRINTED SAFETY SEAL UNDER
CAP IS BROKEN OR MISSING

Satisfaction guaranteed – For questions
or comments please call 1-888-287-1915.

DISTRIBUTED BY: Walmart Inc.,
Bentonville, AR 72716

PRODUCT OF CHINA

*This product is not manufactured or
distributed by Johnson & Johnson
Corporation, owner of the registered
trademark Benadryl® Allergy Ultratabs®.
50844 REV0422B61412

Equate 44-614